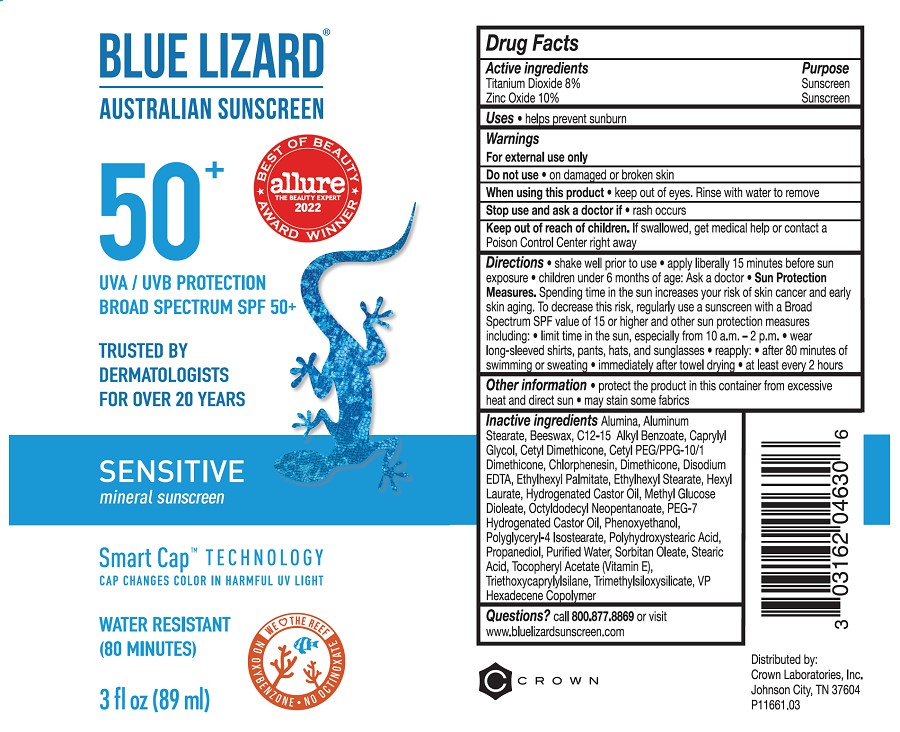 DRUG LABEL: Blue Lizard Sensitive SPF 50 Sunscreen
NDC: 0316-2046 | Form: LOTION
Manufacturer: Crown Laboratories
Category: otc | Type: HUMAN OTC DRUG LABEL
Date: 20260112

ACTIVE INGREDIENTS: TITANIUM DIOXIDE 89.6 mg/1 mL; ZINC OXIDE 112 mg/1 mL
INACTIVE INGREDIENTS: POLYGLYCERYL-4 ISOSTEARATE; PEG-7 HYDROGENATED CASTOR OIL; PHENOXYETHANOL; STEARIC ACID; PROPANEDIOL; WATER; SORBITAN MONOOLEATE; .ALPHA.-TOCOPHEROL ACETATE; HEXADECYL POVIDONE (4 HEXADECYL BRANCHES/REPEAT); DIMETHICONE; TRIMETHYLSILOXYSILICATE (M/Q 0.8-1.0); POLYHYDROXYSTEARIC ACID (2300 MW); CETYL DIMETHICONE 25; ALUMINUM STEARATE; TRIETHOXYCAPRYLYLSILANE; ETHYLHEXYL PALMITATE; ALUMINUM OXIDE; YELLOW WAX; ALKYL (C12-15) BENZOATE; CETYL PEG/PPG-10/1 DIMETHICONE (HLB 5); EDETATE DISODIUM; ETHYLHEXYL STEARATE; CAPRYLYL GLYCOL; HEXYL LAURATE; HYDROGENATED CASTOR OIL; METHYL GLUCOSE DIOLEATE; CHLORPHENESIN; OCTYLDODECYL NEOPENTANOATE

Blue Lizard Sensitive SPF 50 Sunscreen

Active ingredients

Titanium Dioxide 8%

Zinc Oxide 10%

Purpose

Sunscreen

Uses

- helps prevent sunburn

Warnings

For external use only

Do not use

- on damaged or broken skin

When using this product

- keep out of eyes. Rinse with water to remove

Stop use and ask a doctor if

- rash occurs

Keep out of reach of children.

If swallowed, get medical help or contact a Poison Control Center right away

Directions

• shake well prior to use

• Apply liberally 15 minutes before sun exposure

• children under 6 months: Ask a doctor

• Sun Protection Measures. Spending time in the sun increases your risk of skin cancer and early skin aging. To decrease this risk, regularly use a sunscreen with a Broad Spectrum SPF value of 15 or higher and other sun protection measures including: l

- limit time in the sun, especially from 10 a.m. - 2 p.m.
- wear long-sleeved shirts, pants, hats, and sunglasses.

• reapply:

- after 80 minutes of swimming or sweating
- immediately after towel drying
- at least every 2 hours

Other information

- protect the product in this container from excessive heat and direct sun
- may stain some fabrics

Inactive ingredients

Alumina, Aluminum Stearate, Beeswax, C12-15 Alkyl Benzoate, Caprylyl Glycol, Cetyl Dimethicone, Cetyl PEG/PPG-10/1 Dimethicone, Chlorphenesin, Dimethicone, Disodium EDTA, Ethylhexyl Palmitate, Ethylhexyl Stearate, Hexyl Laurate, Hydrogenated Castor Oil, Methyl Glucose Dioleate, Octyldodecyl Neopentanoate, PEG-7 Hydrogenated Castor Oil, Phenoxyethanol, Polyglyceryl-4 Isostearate, Polyhydroxystearic Acid, Propanediol, Purified Water, Sorbitan Oleate, Stearic Acid, Tocopheryl Acetate (Vitamin E), Triethoxycaprylylsilane, Trimethylsiloxysilicate, VP Hexadecene Copolymer

Questions?

Call 800.877.8869 or visit www.bluelizardsunscreen.com

Crown Laboratories, Inc., Johnson City, TN 37604

Blue Lizard Sensitive 3oz Tube

BLUE LIZARD

AUSTRALIAN SUNSCREEN

50+

UVA/UVB PROTECTION

BROAD SPECTRUM SPF 50+

TRUSTED BY DERMATOLOGISTS FOR OVER 20 YEARS

SENSITIVE

mineral sunscreen

Smart Cap TECHNOLOGY

CAP CHANGES COLOR IN HARMFUL UV LIGHT

WATER RESISTANT (80 MINUTES)

3fl oz (89ml)

P11661.03